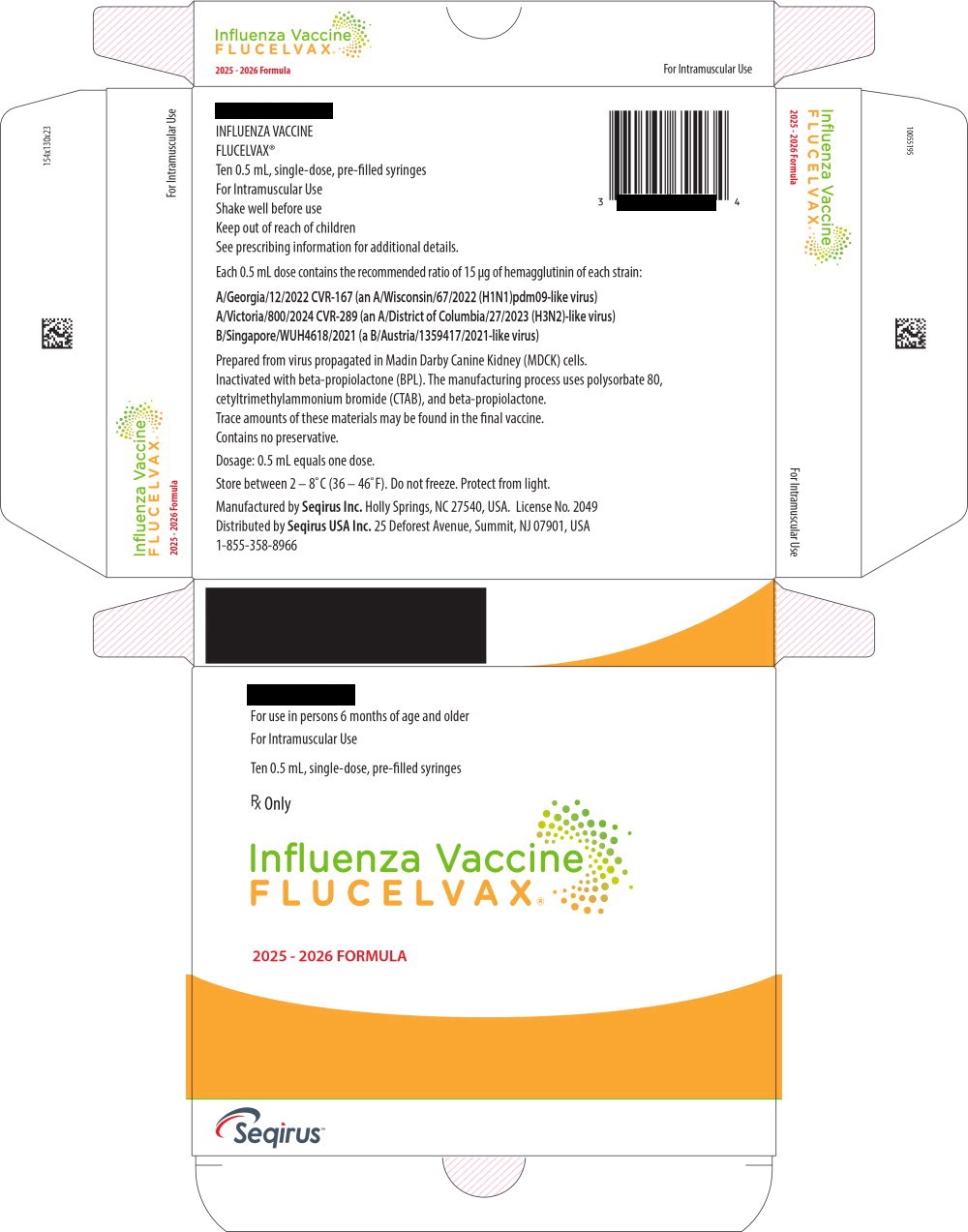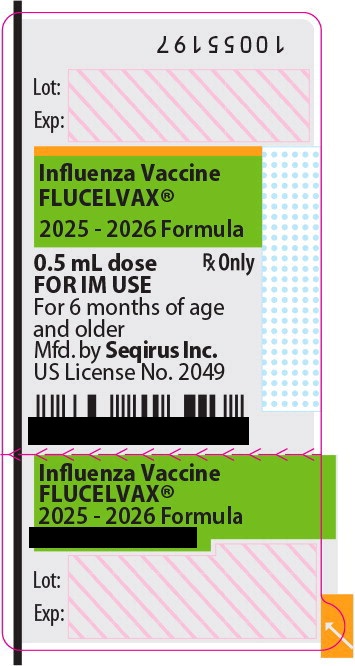 DRUG LABEL: Flucelvax
NDC: 83703-084 | Form: INJECTION, SUSPENSION
Manufacturer: Bamboo US BidCo LLC
Category: other | Type: VACCINE LABEL
Date: 20260202

ACTIVE INGREDIENTS: INFLUENZA A VIRUS A/GEORGIA/12/2022 CVR-167 (H1N1) ANTIGEN (MDCK CELL DERIVED, PROPIOLACTONE INACTIVATED) 15 ug/0.5 mL; INFLUENZA A VIRUS A/VICTORIA/800/2024 CVR-289 (H3N2) ANTIGEN (MDCK CELL DERIVED, PROPIOLACTONE INACTIVATED) 15 ug/0.5 mL; INFLUENZA B VIRUS B/SINGAPORE/WUH4618/2021 ANTIGEN (MDCK CELL DERIVED, PROPIOLACTONE INACTIVATED) 15 ug/0.5 mL
INACTIVE INGREDIENTS: POTASSIUM CHLORIDE; SODIUM CHLORIDE; MAGNESIUM CHLORIDE; SODIUM PHOSPHATE, DIBASIC, DIHYDRATE; POTASSIUM PHOSPHATE, MONOBASIC; WATER

FLUCELVAX (Influenza Vaccine)
Injectable Suspension, for Intramuscular Use
2025-2026 Formula
Initial U.S. Approval: 2012

Principal Display Panel – 0.5 mL Carton Label

For use in persons 6 months of age and older

For Intramuscular Use

Ten 0.5 mL, single-dose, pre-filled syringes

Rx Only

Influenza Vaccine
FLUCELVAX ®

2025 - 2026 FORMULA

Seqirus™

Principal Display Panel – 0.5 mL Syringe Label

Influenza Vaccine
FLUCELVAX ®

2025 - 2026 Formula

0.5 mL dose

Rx Only

FOR IM USE

For 6 months of age and older